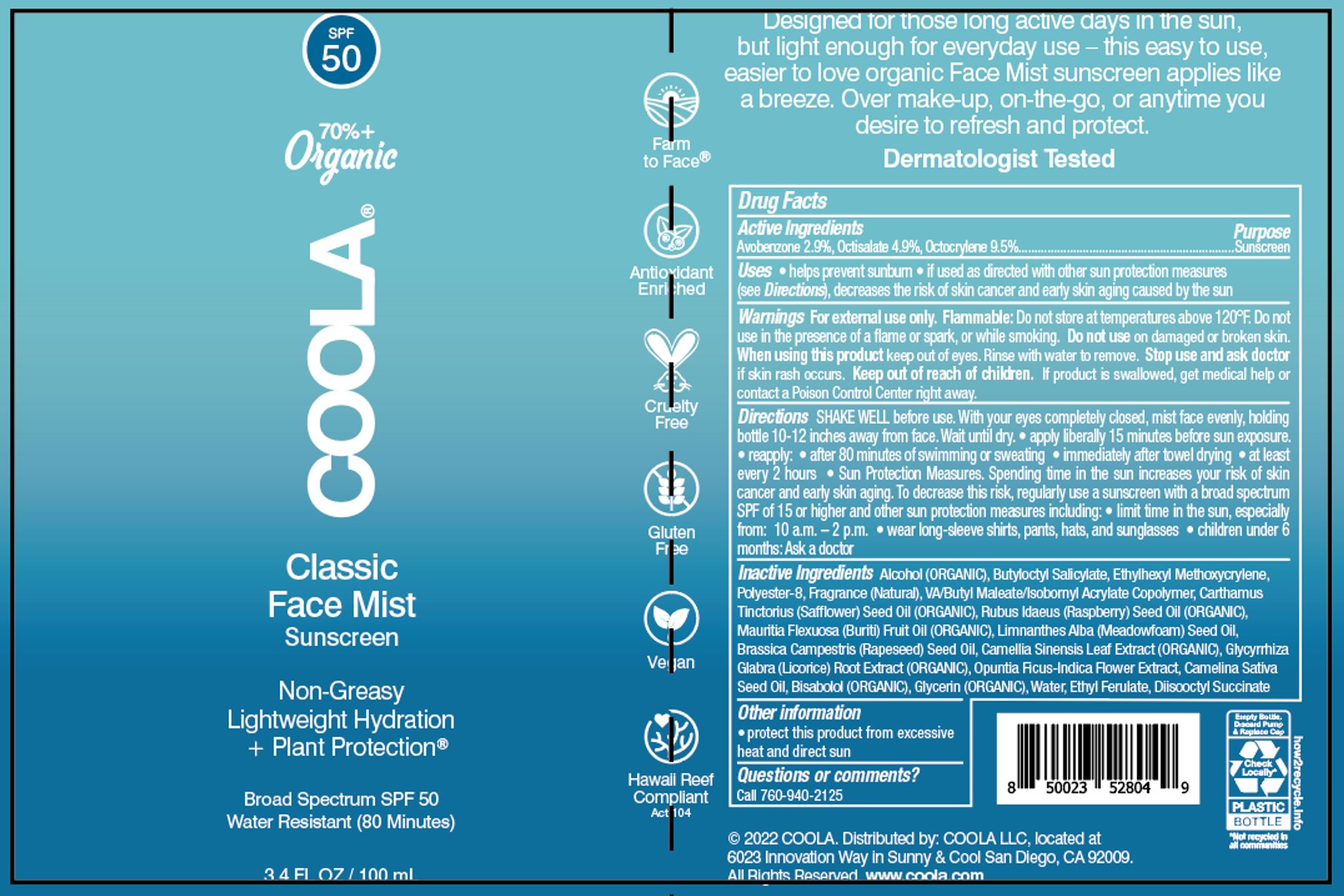 DRUG LABEL: Coola
NDC: 79753-033 | Form: SPRAY
Manufacturer: COOLA LLC
Category: otc | Type: HUMAN OTC DRUG LABEL
Date: 20241220

ACTIVE INGREDIENTS: AVOBENZONE 2.9 g/100 mL; OCTISALATE 4.9 g/100 mL; OCTOCRYLENE 9.5 g/100 mL
INACTIVE INGREDIENTS: ALCOHOL; POLYESTER-8 (1400 MW, CYANODIPHENYLPROPENOYL CAPPED); SAFFLOWER OIL; ETHYLHEXYL METHOXYCRYLENE; VINYL ACETATE; ISOBORNYL ACRYLATE; DIBUTYL MALEATE; CAMELINA SATIVA SEED OIL; DICAPRYL SUCCINATE; BRASSICA RAPA SUBSP. OLEIFERA OIL; GREEN TEA LEAF; MAURITIA FLEXUOSA FRUIT OIL; LEVOMENOL; ETHYL FERULATE; MEADOWFOAM SEED OIL; OPUNTIA FICUS-INDICA FLOWER; RASPBERRY SEED OIL; GLYCYRRHIZA GLABRA; WATER; GLYCERIN; BUTYLOCTYL SALICYLATE

Coola Classic Face Sunscreen Mist SPF 50 (07-OC-013)

Active Ingredients

Avobenzone 2.9%, Octisalate 4.9%, Octocrylene 9.5%

Purpose

Sunscreen

Uses

Helps prevent sunburn

If used as directed with other sun protection measures (see Directions), decreases the risk of skin cancer and early skin aging caused by the sun.

Warnings

For external use only.

Flammable: Do not store at temperatures above 120 F.

Do not use in the presence of a flame or spark, or while smoking.

Do not use on damaged or broken skin.

When using this product keep out of eyes. Rinse with water to remove.

Stop use and ask doctor if skin rash occurs.

.

Keep out of reach of children.

If product is swallowed, get medical help or contact a Poison Control Center right away

Directions

SHAKE WELL before use.

With your eyes completely closed, mist face evenly, holding bottle 10-12 inches away from face.

Wait until dry.

Apply liberally 15 minutes before sun exposure.

Reapply:

-After 80 minutes minutes of swimming or sweating

-Immediately after towel drying

-At least every 2 hours

Sun Protection Measures: Spending time in the sun increases your risk of skin cancer and early skin aging. To decrease the risk, regularly use a sunscreen with a broad-spectrum SPF of 15 or higher and other protection measures including:

-Limit time in the sun, especially from 10 a.m. – 2 p.m.

-Wear long sleeves shirts, pants, hats, and sunglasses.

Children under 6 months: Ask a doctor.

Inactive Ingredients

Alcohol (ORGANIC), Butyloctyl Salicylate, Ethylhexyl Methoxycrylene, Polyester-8, Fragrance (Natural), VA/Butyl Maleate/Isobornyl Acrylate Copolymer, Carthamus Tinctorius (Safflower) Seed Oil (ORGANIC), Rubus Idaeus (Raspberry) Seed Oil (ORGANIC), Mauritia Flexuosa (Buriti) Fruit Oil (ORGANIC), Limnanthes Alba (Meadowfoam) Seed Oil, Brassica Campestris (Rapeseed) Seed Oil, Camellia Sinensis Leaf Extract (ORGANIC),Glycyrrhiza Glabra (Licorice) Root Extract (ORGANIC), Opuntia Ficus-Indica Flower Extract, Camelina Sativa Seed Oil, Bisabolol (ORGANIC), Glycerin (ORGANIC), Water, Ethyl Ferulate, Diisooctyl Succinate

Other Information

Protect this product from excessive heat and direct sun

Questions or Comments

Call 760-940-2125